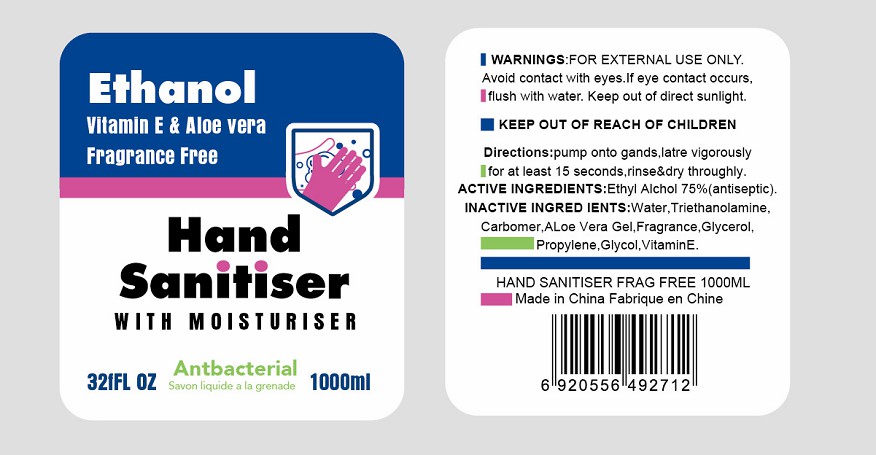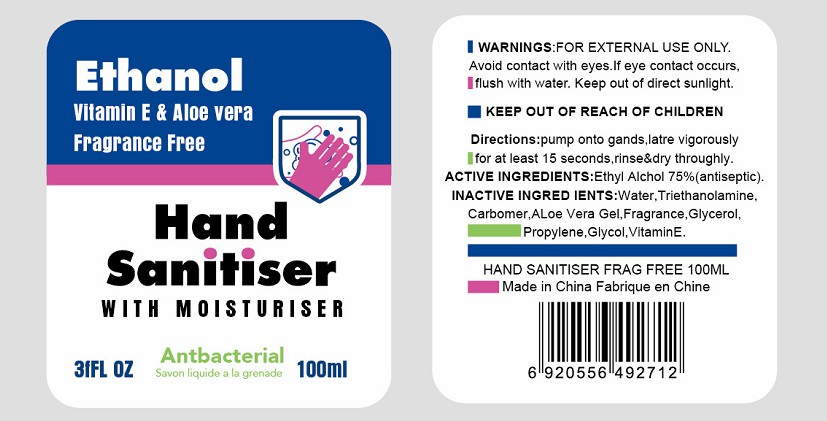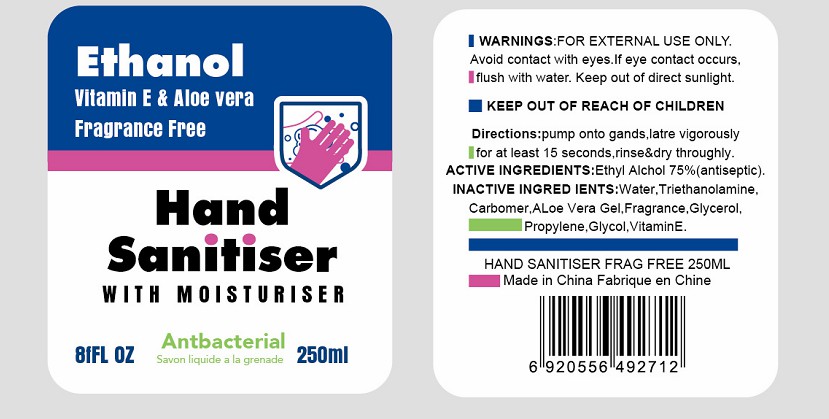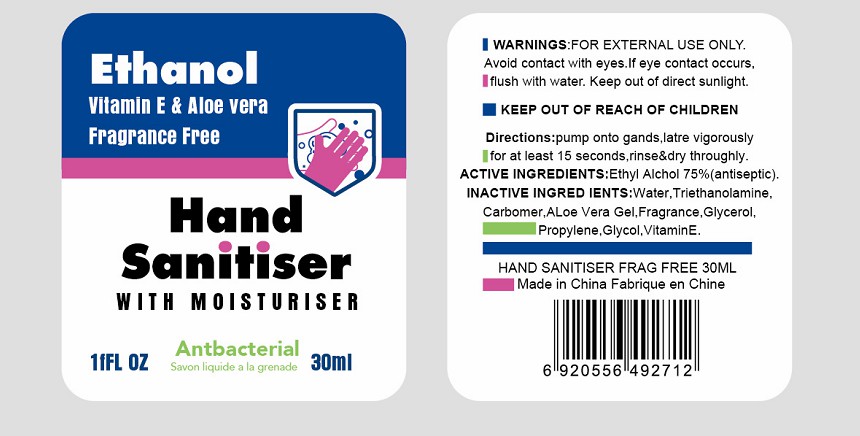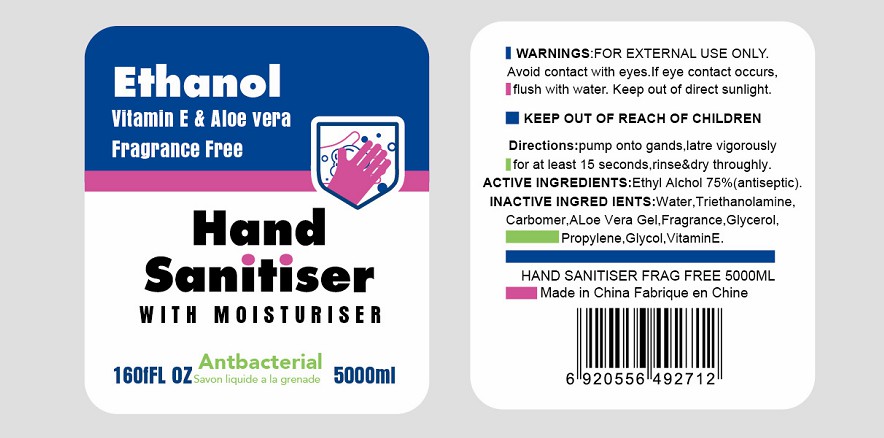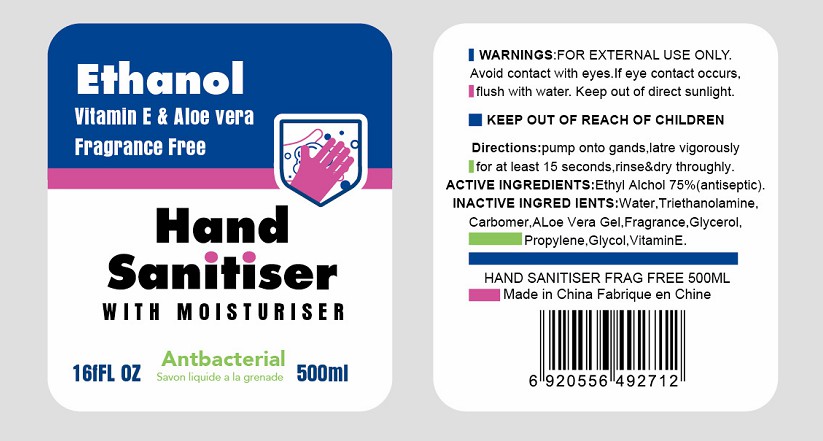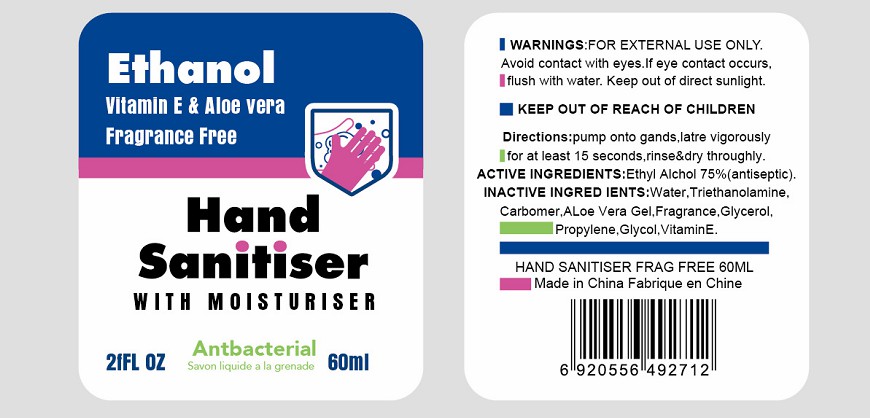 DRUG LABEL: Hand santiser
NDC: 76881-005 | Form: GEL
Manufacturer: Yiwu city jieyi cleaning supplies co., LTD
Category: otc | Type: HUMAN OTC DRUG LABEL
Date: 20200514

ACTIVE INGREDIENTS: ALCOHOL 75 mL/100 mL
INACTIVE INGREDIENTS: 1-O-(2-METHOXY-4-HEXADECENYL)GLYCEROL; .ALPHA.-TOCOPHEROL SUCCINATE, DL-; DETOSU/TRIETHYLENE GLYCOL/TRIETHYLENE GLYCOL POLYGLYCOLIDE COPOLYMER; ALOE VERA LEAF; 3-(P-METHOXYPHENYL)PROPYLENE-1,2-OXIDE; FRAGRANCE LAVENDER & CHIA F-153480; TROLAMINE; CARBOMER 1342; WATER

This is a hand sanitizer manufactured according to the Temporary Policy for Preparation of Certain Alcohol-Based Hand Sanitizer Products During the Public Health Emergency (CoViD-19); Guidance for Industry.

The hand sanitizer is manufactured using only the following United States Pharmacopoeia (USP) grade ingredients in the preparation of the product (percentage in final product formulation) consistent with World Health Organization (WHO) recommendations:

1. Isopropyl Alcohol (75%, v/v) in an aqueous solution denatured according to Alcohol and Tobacco Tax and Trade Bureau regulations in 27 CFR part 20.
2. Glycerol (1.45% v/v).
3. Hydrogen peroxide (0.125% v/v).
4. Sterile distilled water or boiled cold water.

The firm does not add other active or inactive ingredients. Different or additional ingredients may impact the quality and potency of the product.

Active Ingredient(s)

Ethyl Alchol 75%(antiseptic）

Purpose

/

Use

/

Warnings

FOR EXTERNAL USE ONLY
Avoid contact with eyes. If eye contact occurs, flush with water. Keep out of direct sunligh.

Do not use

/

WHEN USING

/

STOP USE

/

KEEP OUT OF REACH OF CHILDREN

Directions

pump onto gands, latre vigorously for at least 15 seconds, rinse&dry throughly.

Inactive ingredients

Water, TriethanolamineCarbomer, ALoe vera Gel, Fragrance, Glycerol, Propylene, Glycol, VitaminE

Package Label - Principal Display Panel

/